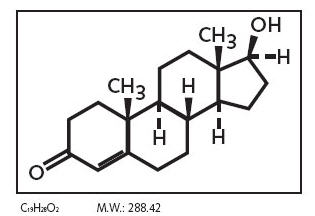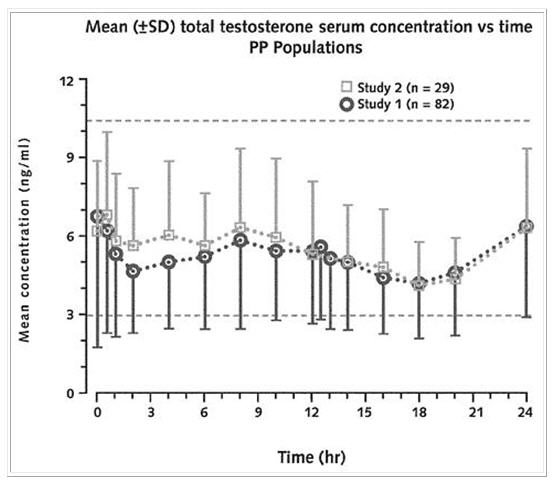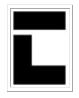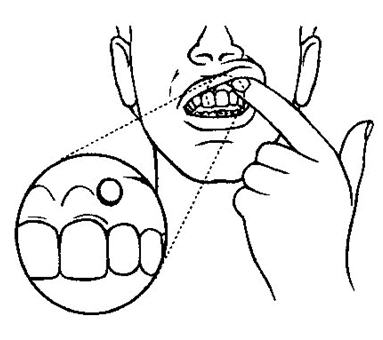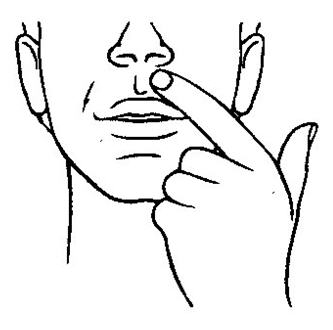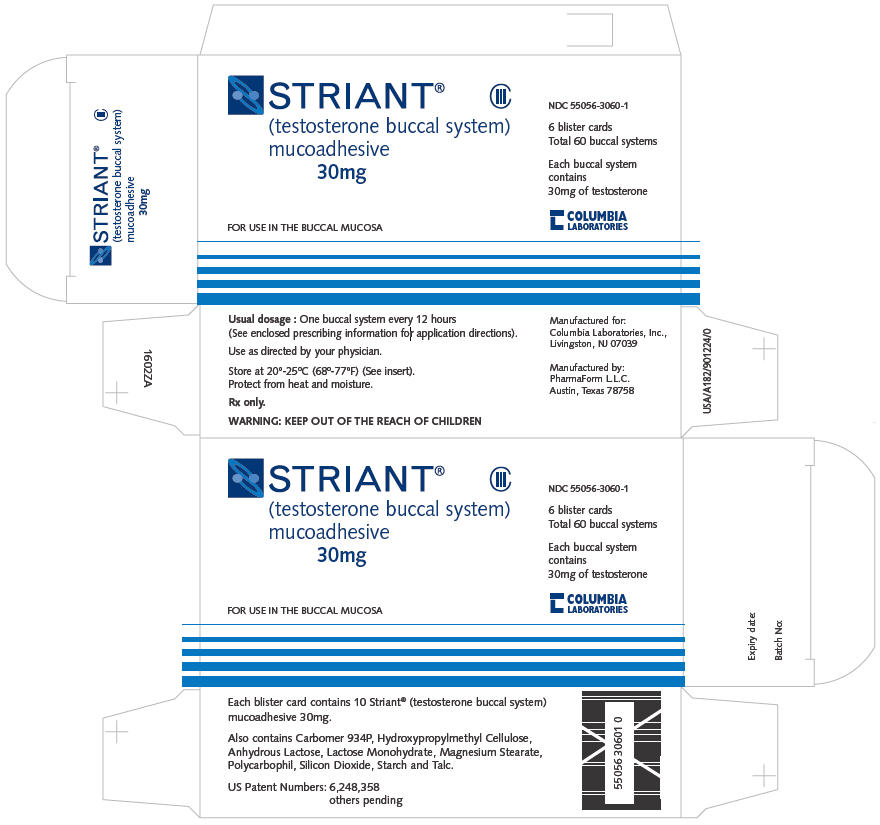 DRUG LABEL: Striant
NDC: 55056-3060 | Form: TABLET
Manufacturer: Columbia Laboratories, Inc.
Category: prescription | Type: HUMAN PRESCRIPTION DRUG LABEL
Date: 20091119
DEA Schedule: CIII

ACTIVE INGREDIENTS: testosterone 30 mg/1 1
INACTIVE INGREDIENTS: anhydrous lactose; carbomer 934; hypromellose; magnesium stearate ; lactose monohydrate; polycarbophil; silicon dioxide; starch, corn; talc

STRIANT® (testosterone buccal system)
mucoadhesive

DESCRIPTION

Striant® (testosterone buccal system) is designed to adhere to the gum or inner cheek. It provides a controlled and sustained release of testosterone through the buccal mucosa as the buccal system gradually hydrates. Insertion of Striant® twice a day, in the morning and in the evening, provides continuous systemic delivery of testosterone.

Striant® is a white to off-white colored, monoconvex, tablet-like, mucoadhesive buccal system. Striant® adheres to the gum tissue above the incisors, with the flat surface facing the cheek mucosa.

The active ingredient in Striant® is testosterone. Each buccal system contains 30 mg of testosterone. Testosterone USP is practically white crystalline powder chemically described as 17-beta hydroxyandrost-4-en-3one.

Chemical Structure:

Other pharmacologically inactive ingredients in Striant® are anhydrous lactose NF, carbomer 934P, hypromellose USP, magnesium stearate NF, lactose monohydrate NF, polycarbophil USP, colloidal silicon dioxide NF, starch NF and talc USP.

CLINICAL PHARMACOLOGY

Striant® delivers physiologic amounts of testosterone to the systemic circulation, thereby producing circulating testosterone concentrations in hypogonadal males that approximate physiologic levels seen in healthy young men (300 - 1050 ng/dL).

Testosterone - General Androgen Effects

Endogenous androgens, including testosterone and dihydrotestosterone (DHT) are responsible for the normal growth and development of the male sex organs and for maintenance of secondary sex characteristics. These effects include the growth and maturation of prostate, seminal vesicles, penis, and scrotum; the development of male hair distribution, such as facial, pubic, chest, and axillary hair; laryngeal enlargement, vocal chord thickening, and alterations in body musculature and fat distribution. Testosterone and DHT are necessary for the normal development of secondary sex characteristics.

Male hypogonadism results from insufficient production of testosterone and is characterized by low serum testosterone concentrations. Symptoms associated with male hypogonadism include impotence and decreased sexual desire, fatigue and loss of energy, mood depression, regression of secondary sexual characteristics and osteoporosis. Hypogonadism is a risk factor for osteoporosis in men.

Drugs in the androgen class also promote retention of nitrogen, sodium, potassium, phosphorus, and decreased urinary excretion of calcium. Androgens have been reported to increase protein anabolism and decrease protein catabolism. Nitrogen balance is improved only when there is sufficient intake of calories and protein.

Androgens are responsible for the growth spurt of adolescence and for the eventual termination of linear growth brought about by fusion of the epiphyseal growth centers. In children, exogenous androgens accelerate linear growth rates but may cause a disproportionate advancement in bone maturation. Use by children and adolescents over long periods may result in fusion of the epiphyseal growth centers and termination of the growth process. Androgens have been reported to stimulate the production of red blood cells by enhancing the production of erythropoietin.

During exogenous administration of androgens, endogenous testosterone release may be inhibited through feedback inhibition of pituitary luteinizing hormone (LH). At large doses of exogenous androgens, spermatogenesis may also be suppressed through feedback inhibition of pituitary follicle-stimulating hormone (FSH).

Pharmacokinetics

Absorption

When applied to the buccal mucosa, Striant® slowly releases testosterone, allowing for absorption of testosterone through gum and cheek surfaces that are in contact with the buccal system. Since venous drainage from the mouth is to the superior vena cava, trans-buccal delivery of testosterone circumvents first-pass (hepatic) metabolism.

Following the initial application of Striant®, the serum testosterone concentration rises to a maximum within 10-12 hours. The mean maximum (C max) and mean average serum total testosterone concentrations for the 12 hour dosing period (C avg(0-12)) are within the normal physiologic range.

Striant® is intended for twice daily dosing. Serum concentrations of testosterone reach steady-state levels after the second dose of twice daily Striant® dosing. Following removal of Striant®, the serum testosterone concentration decreases to a level below the normal range within 2-4 hours.

With twice-daily repeated dosing, mean pharmacokinetic parameters at steady-state for total testosterone serum concentration were very similar between studies of 7-day and 12-week dosing durations. Mean C avg(0-24) across the studies ranged from 520 to 550 ng/dL and these mean values were within the physiologic range (see Table 1).

Table 1. Mean (±SD) Steady-State Serum Total Testosterone Concentrations During Treatment with Striant® (on Final Day of Treatment)
 | Study 1 | Study 2
 | 12-weeks (N=82) | 7-days (N=29)
C avg(0-24) (ng/dL) | 520 (±205) | 550 (±169)
C max(0-24) (ng/dL) | 970 (±442) | 910 (±319)
C min(0-24) (ng/dL) | 290 (±130) | 320 (±131)

Although no specific food effect study was conducted, pivotal Phase 3 study results showed that consumption of food and beverage did not significantly affect the absorption of testosterone from Striant®.

The effects of toothbrushing, mouthwashing, chewing gum and alcoholic beverages on the use and absorption of Striant® were not investigated in controlled studies, however, Phase 3 clinical studies permitted patients to do these activities indicating the use of Striant® was not significantly affected by these activities.

Distribution

Circulating testosterone is chiefly bound in the serum to sex hormone-binding globulin (SHBG) and albumin. The albumin-bound fraction of testosterone easily dissociates from albumin and is presumed to be bioactive. The portion of testosterone bound to SHBG is not considered biologically active. The amount of SHBG in the serum and the total testosterone level will determine the distribution of bioactive and nonbioactive androgen. SHBG-binding capacity is high in prepubertal children, declines during puberty and adulthood, and increases again during the later decades of life. Approximately 40% of testosterone in plasma is bound to SHBG, 2% remains unbound (free) and the rest is bound to albumin and other proteins.

Metabolism

There is considerable variation in the half-life of testosterone as reported in the literature, ranging from ten to 100 minutes. Testosterone is metabolized to various 17-keto steroids through two different pathways, and the major active metabolites are estradiol and dihydrotestosterone (DHT). DHT binds with greater affinity to SHBG than does testosterone. In many tissues the activity of testosterone appears to depend on reduction to DHT, which binds to cytosol receptor proteins. The steroid-receptor complex is transported to the nucleus where it initiates transcription and cellular changes related to androgen action. In reproductive tissues, DHT is further metabolized to 3-alpha and 3-beta androstanediol.

Mean DHT concentrations increase in parallel with testosterone concentrations during Striant® treatment. After 24 hours of treatment, mean DHT serum concentrations are within normal range. The mean steady-state T/DHT ratio during treatment with Striant® remained within normal limits as determined by the analytical laboratory involved with the clinical trials. These ratios ranged from approximately 9-12.

Excretion

About 90% of a dose of testosterone given intramuscularly is excreted in the urine as glucuronic and sulfuric acid conjugates of testosterone and its metabolites; about 6% of a dose is excreted in the feces, mostly in the unconjugated form. Inactivation of testosterone occurs primarily in the liver.

Special Populations

No formal studies were conducted comparing the pharmacokinetics of testosterone in different racial groups or in compromised patients with renal or hepatic insufficiencies.

Clinical Studies

Striant® was evaluated in a multicenter, open-label, single arm, Phase 3 trial in 98 hypogonadal men (Study 1). In this study, Striant® was administered twice daily for 12 weeks. The mean age was 53.6 years (range 20 to 75 years). Overall, 68 (69.4%) patients were Caucasian, 9 (9.2%) were African-American, 15 (15.3%) were Hispanic, 4 (4.1%) were Asian, and 2 (2.0%) were of another ethnic origin. At baseline, ten patients (10.2%) reported current use of tobacco and forty-one (41.8%) drank alcohol. Of 82 patients who completed the trial and had sufficient data for full analysis, 86.6% had mean serum testosterone concentration (C avg(0-24)) values within the physiologic range.

The mean (±SD) time-averaged steady-state daily testosterone concentration (C avg(0-24)) at Week 12 was 520 (±205) ng/dL compared with a mean of 149 (±99) ng/dL at Baseline. At Week 12, the mean percentage of time over the 24-hour sampling period that total testosterone concentrations remained within the normal range of 300 - 1050 ng/dL was 76%. Table 1 above provides the steady-state serum testosterone concentrations in greater detail.

Striant® was also evaluated in a 7-day multicenter, open-label, parallel study comparing Striant® and an approved testosterone transdermal system (Study 2). In this study, Striant® was again administered twice daily. On Day 7, the mean C avg(0-24) for the 29 patients who received Striant® was 550 (±169) ng/dL compared with a mean of 119 (±78) ng/dL at Baseline. At Day 7, the mean percentage of time for Striant® over the 24-hour sampling period that testosterone concentrations remained within the physiologic range of 300-1050 ng/dL was 84%. Additional pharmacokinetic data for this study are presented in Table 1 above.

Figure 1 below shows the mean total testosterone serum concentration versus time at steady-state for two representative consecutive dosing intervals from both the 7-day and 12 week studies. The figure shows that the concentration-time curves for the different duration studies are consistent.

Figure 1: Mean (SD) total testosterone concentration-time curves for two consecutive dosing intervals at steady-state for both the 12- week study (Study 1) and the 7-day study (Study 2) of Striant®. (The horizontal dotted lines represent the upper and lower limit of normal for the normal physiologic range in healthy adult males).

In both clinical trials, mean DHT concentrations increased in parallel with testosterone concentrations, with the total testosterone/DHT ratio (9 - 12) indicating no alteration in metabolism of testosterone to DHT in testosterone deficient men treated with Striant® as compared with young, healthy eugonadal men.

During continuous treatment there was no accumulation of testosterone, and mean total testosterone, free testosterone, and DHT were maintained within their physiologic ranges.

INDICATIONS AND USAGE

Striant® is indicated for replacement therapy in males for conditions associated with a deficiency or absence of endogenous testosterone:

Primary hypogonadism (congenital or acquired) - testicular failure due to cryptorchidism, bilateral torsion, orchitis, vanishing testis syndrome, orchidectomy, Klinefelter's syndrome, chemotherapy, or toxic damage from alcohol or heavy metals. These men usually have low serum testosterone levels and gonadotropins (FSH, LH) above the normal range.

Hypogonadotropic hypogonadism (congenital or acquired) -- idiopathic gonadotropin or LHRH deficiency, or pituitary hypothalamic injury from tumors, trauma, or radiation. These patients have low serum testosterone levels but have gonadotropins in the normal or low range.

CONTRAINDICATIONS

Androgens are contraindicated in men with carcinoma of the breast or known or suspected carcinoma of the prostate.

Striant® is not indicated for use in women, and must not be used in women. Testosterone supplements may cause fetal harm.

Striant® should not be used in patients with known hypersensitivity to any of its ingredients, including testosterone USP that is chemically synthesized from soy.

WARNINGS

1. Prolonged use of high doses of orally active 17-alpha-alkyl androgens (e.g., methyltestosterone) have been associated with serious hepatic adverse effects (peliosis hepatis, hepatic neoplasms, cholestatic hepatitis, and jaundice). Peliosis hepatis can be a life-threatening or fatal complication. Long-term therapy with testosterone enanthate, which elevates blood levels for prolonged periods, has produced multiple hepatic adenomas. Testosterone is not known to produce these adverse effects.
2. Geriatric patients treated with androgens may be at an increased risk for the development of prostatic hyperplasia and prostatic carcinoma.
3. Geriatric patients and other patients with clinical or demographic characteristics that are recognized to be associated with an increased risk of prostate cancer should be evaluated for the presence of prostate cancer prior to initiation of testosterone replacement therapy. In men receiving testosterone replacement therapy, surveillance for prostate cancer should be consistent with current practices for eugonadal men (see PRECAUTIONS: Carcinogenesis, Mutagenesis, Impairment of Fertility and Laboratory Tests).
4. Edema with or without congestive heart failure may be a serious complication in patients with preexisting cardiac, renal, or hepatic disease. In addition to discontinuation of the drug, diuretic therapy may be required.
5. Gynecomastia frequently develops and occasionally persists in patients being treated for hypogonadism.
6. The treatment of hypogonadal men with testosterone esters may potentiate sleep apnea in some patients especially those with risk factors such as obesity or chronic lung diseases.

PRECAUTIONS

Striant® is applied to the upper gum just above the incisor tooth on either side of the mouth. Long-term data on gum safety is available for 117 patients and 51 patients with at least 6 months and 1 year of exposure, respectively. While the available data supports the overall oral safety of Striant®, longer-term data is not currently available and studies continue. Until such longer-term data become available, it is recommended that patients regularly inspect their own gum region where Striant® is applied. Any abnormal finding should be brought promptly to the attention of the patient's physician. In such circumstances, dental consultation may be appropriate.

General

The physician should instruct patients to report any of the following:

- Too frequent or persistent erections of the penis.
- Any nausea, vomiting, changes in skin color, or ankle swelling.
- Breathing disturbances, including those associated with sleep.

Information for Patients

Advise patients to carefully read the attached patient leaflet accompanying each carton of Striant® blister packaged tablets.

Advise patients to regularly inspect the gum region where they apply Striant® and to report any abnormality to their health care professional.

Laboratory Tests

1. Hemoglobin and hematocrit levels should be checked periodically (to detect polycythemia) in patients on long-term androgen therapy.
2. Liver function, prostate specific antigen (PSA), cholesterol and high-density lipoprotein should be checked periodically.
3. Serum total testosterone concentrations may be checked four to twelve weeks after initiating treatment with Striant®. To capture the maximum serum concentration, an early morning sample (just prior to applying the A.M. dose) is recommended. In the infrequent circumstance where the total testosterone concentration in this sample is excessive, therapy with Striant® should be discontinued and an alternative treatment considered.

Drug interactions

Oxyphenbutazone

Concurrent administration of oxyphenbutazone and androgens may result in elevated serum levels of oxyphenbutazone.

Insulin

In diabetic patients, the metabolic effects of androgens may decrease blood glucose and therefore, insulin requirements.

Corticosteroids

Concurrent administration of testosterone with ACTH or corticosteroids may enhance edema formation and should be administered cautiously, particularly in patients with cardiac or hepatic disease.

Drug/Laboratory Test Interactions

Androgens may decrease levels of thyroxin-binding globulin, resulting in decreased total T4 serum levels and increased resin uptake of T3 and T4. Free thyroid hormone levels remain unchanged, however, and there is no clinical evidence of thyroid dysfunction.

Carcinogenesis, mutagenesis, impairment of fertility

Animal data

Testosterone has been tested by subcutaneous injection and implantation in mice and rats. In mice, the implant induced cervical-uterine tumors, which metastasized in some cases. There is suggestive evidence that injection of testosterone into some strains of female mice increases their susceptibility to hepatoma. Testosterone is also known to increase the number of tumors and decrease the degree of differentiation of chemically induced carcinomas of the liver in rats.

Human data

There were rare reports of hepatocellular carcinoma in patients receiving long-term therapy with androgens in high doses. Withdrawal of the drugs did not lead to regression of the tumors in all cases.

Striant® has been evaluated in patients for 1 year without reports of cancer related to the product. However, safety in patients beyond 1 year has not been established.

Geriatric patients treated with androgens may be at an increased risk for the development of prostatic hyperplasia and prostatic carcinoma.

Geriatric patients and other patients with clinical or demographic characteristics that are recognized to be associated with an increased risk of prostate cancer should be evaluated for the presence of prostate cancer prior to initiation of testosterone replacement therapy.

In men receiving testosterone replacement therapy, surveillance for prostate cancer should be consistent with current practices for eugonadal men.

Pregnancy Category X

(see CONTRAINDICATIONS)

Teratogenic Effects

Striant® is not indicated for women and must not be used in women.

Labor and Delivery

Striant® is not indicated for women and must not be used in women.

Nursing Mothers

Striant® is not indicated for women and must not be used in women.

Pediatric Use

Safety and effectiveness in pediatric male patients below the age of 18 have not yet been established

Geriatric Use

Of the total number of subjects in clinical studies of Striant®, 51 patients (16.5 percent) were 65 and over. No overall differences in safety or effectiveness were observed between these subjects and younger subjects. However, in Study 1, in patients 65 years of age and older, the total testosterone C avg(0-24) value was higher by 12.7% compared to patients less than 65 years of age. In addition, the total T to DHT area-under-the curve ratio was lower in the older population compared to the younger population by 15.6%. These differences may not be clinically significant.

ADVERSE REACTIONS

In all clinical studies combined, a total of 308 patients were treated with Striant® for up to 12 months

Twelve Week Trials

In the pivotal, Phase 3, open-label controlled study (Study 1), 98 patients received Striant® for up to 12 weeks. Adverse events judged possibly, probably, or definitely related to the use of Striant® and reported by >/= 1% of patients in Study 1 are listed in Table 2.

Table 2. Incidences of Adverse Events Possibly, Probably or Definitely Related Use of Striant® in Study 1
Adverse event | Striant® (n=98)
Gum or Mouth Irritation | 9.2%
Taste Bitter | 4.1%
Gum Pain | 3.1%
Gum Tenderness | 3.1%
Headache | 3.1%
Gum Edema | 2.0%
Taste Perversion | 2.0%

Please see "Gum-related adverse events and gum examinations" subsection for further information. The majority of gum-related adverse events were transient. Gum irritation generally resolved in 1 to 8 days. Gum tenderness resolved in 1 to 14 days.

The following adverse events judged possibly, probably or definitely related to the use of Striant® occurred in 1 patient each in Study 1: abdominal cramp, acne, anxiety, asthma (acute), breast enlargement, breast pain, buccal mucosal roughening, difficulty in micturition, fatigue, gingivitis, gum blister, gustatory sense diminished, hematocrit increased, lipids serum increased, liver function tests abnormal, nose edema, stinging of lips, and toothache.

There was one additional 12-week study in 12 patients. In this study, additional adverse events judged at least possibly related to Striant® and reported by 1 patient each included emotional lability and hypertension.

Long-Term Extension Trials

In two long-term extension trials, a total of 117 and 51 patients received Striant® for at least 6 months and 1 year, respectively.

Of 117 patients treated for at least 6 months, adverse events judged possibly, probably, or definitely related to treatment and reported by 1 patient each included: anxiety, buccal inflammation, depression, dry mouth, gastrointestinal disorder, gum redness, hypertension, infection, medication error, nausea, pruritis, renal function abnormal, stomatitis, taste bitter, taste perversion, and toothache. Polycythemia and increased serum prostate specific antigen (PSA) were reported in three and two patients, respectively.

Adverse events reported in the 51 patients treated for at least one year were similar to those reported after 6 months of treatment and lower in incidence.

Gum-related adverse events and gum examinations

In the pivotal controlled study (Study 1), all reported gum-related adverse events were collected and gum examinations were conducted at Baseline and every month thereafter.

In Study 1, a total of 16 patients reported 19 gum-related adverse events. Of these, ten patients (10.2%) reported 12 events of mild intensity, four patients (4.1%) reported 5 events of moderate intensity, and two patients (2.0%) reported 2 events of severe intensity. Most of these events were judged probably or definitely related to treatment with Striant®. Four patients (4.1%) discontinued treatment with Striant® due to gum or mouth-related adverse events including two with severe gum irritation, one with mouth irritation, and one with "bad taste in mouth". The majority of gum-related adverse events were transient. Gum irritation generally resolved in 1 to 8 days. Gum tenderness resolved in 1 to 14 days.

In Study 1, monthly gum examinations were conducted to assess for gingivitis, gum edema, oral lesions, ulcerations or leukoplakia. No cases of ulceration or leukoplakia were observed. No new oral lesions were observed. Gingivitis was common at Baseline (32.6%), and was reduced at Week 4 (10.2%), Week 8 (10.2%) and Week 12 (11.2%). Similar findings were seen for gum edema.

In the two long-term extension trials, gum examinations were conducted every 3 months while on treatment. In one of these trials, no patient had a gum abnormality, and in the other trial, moderate gingivitis and mild gum edema were reported by 1 patient each.

DRUG ABUSE AND DEPENDENCE

Striant® contains testosterone, a Schedule III controlled substance as defined by the Anabolic Steroids Control Act.

OVERDOSAGE

There is one report of acute overdosage with testosterone enanthate injection: testosterone levels of up to 11,400 ng/dL were implicated in a cerebrovascular accident.

Oral ingestion of Striant® is not expected to result in clinically significant serum testosterone concentrations due to extensive first-pass (hepatic) metabolism.

DOSAGE AND ADMINISTRATION

The recommended dosing schedule for Striant® is the application of one buccal system (30 mg) to the gum region twice daily; morning and evening (about 12 hours apart). Striant® should be placed in a comfortable position just above the incisor tooth (on either side of the mouth). With each application, Striant® should be rotated to alternate sides of the mouth.

Upon opening the packet, the rounded side surface of the buccal system should be placed against the gum and held firmly in place with a finger over the lip and against the product for 30 seconds to ensure adhesion. Striant® is designed to stay in position until removed. If the buccal system fails to properly adhere to the gum or should fall off during the 12-hour dosing interval, the old buccal system should be removed and a new one applied. If the buccal system falls out of position within 4 hours prior to the next dose, a new buccal system should be applied and it may remain in place until the time of next regularly scheduled dosing.

Patients should take care to avoid dislodging the buccal system. Patients should check to see if Striant® is in place following toothbrushing, use of mouthwash and consumption of food or alcoholic/non-alcoholic beverages. Striant® should not be chewed or swallowed. To remove Striant®, gently slide it downwards from the gum towards the tooth to avoid scratching the gum.

HOW SUPPLIED

Striant® (testosterone buccal system) is for buccal administration only. It contains testosterone, a Schedule III controlled substance as defined by the Anabolic Steroids Control Act.

Striant® is supplied in transparent blister packs containing 10 doses. It is white to off- white colored with a flat edge on one side and a convex surface on the other.

Striant® is debossed on its flat side, as shown below:

Each Striant® buccal system contains 30 mg of testosterone and is supplied as follows:

NDC Number | Strength | Package Size
55056-3060-1 | 30 mg | 6 blister packs, 10 buccal systems per blister; 30 mg per buccal system

Storage and Disposal

Store at 20-25 °C (68-77 °F) [see USP Controlled Room temperature]. Protect from heat and moisture. Damaged blister packages should not be used. Discarded Striant® buccal systems should be disposed of in household trash in a manner that prevents accidental application or ingestion by children or pets.

Rx Only

Manufactured by: Mipharm S.p.A. Milan, Italy

Manufactured for: Columbia Laboratories, Inc. Livingston, NJ 07039

US Patent Numbers: 6,248,358

others pending

PHYSTN002/41005010002
USA/930987/0

Patient Information

STRIANT® CIII
(testosterone buccal system) mucoadhesive

Read the Patient Information that comes with Striant® [STRI' ant] before you start using it and each time you get a refill. There may be new information. This information does not take the place of information from your healthcare provider about your medical condition or your treatment.

What is Striant®?

Striant® is a hormone medicine that contains testosterone. It is used to treat adult men when their bodies do not make any testosterone or not enough testosterone (hypogonadism). Striant® is a white to off-white tablet-like buccal system that is applied to the upper gum area of the mouth. Striant® is not to be chewed or swallowed.

Striant® is a controlled substance (CIII) because it contains testosterone. Therefore, you should keep your Striant® in a secure place. Do not share or sell your Striant®.

Who should not use Striant®?

Do not use Striant® if you:

- have breast cancer (rare in men).
- have prostate cancer.
- are a woman (especially if you are pregnant or breast-feeding). Striant may harm the babies of pregnant and breast-feeding women.
- are allergic to Striant®. The active ingredient in Striant® is testosterone USP. See the end of this leaflet for a list of all ingredients in Striant®.

Tell your doctor if you have or had:

- problems urinating due to an enlarged prostate.
- liver problems.
- kidney problems.
- heart problems.
- lung problems.
- diabetes.
- weight problems (obesity).

Tell your doctor about all the medicines you take, including prescription and non-prescription medicines, vitamins, and herbal supplements. Some medicines may cause serious side effects if taken while you also take Striant®. Some medicines may affect how Striant® works, or Striant® may affect how your other medicines work. Be sure to tell your doctor if you use insulin for diabetes. Your dose of insulin may need to be adjusted if you use Striant®.

How should I use Striant®?

Use Striant® twice a day, once in the morning and once at night (about 12 hours apart). You may find it convenient to apply morning dose after brushing your teeth following breakfast and evening dose following your evening meal.

Striant® should be applied as follows:

- Tear off individual unit then start at the corner tab and peel off paper backing. Push buccal system through foil from the front. You will notice that Striant® is curved on one side and flat on the other side. The flat side has a marking on it (company logo).
- Before you apply Striant®, locate the area on your upper gum, just above either the left or right incisor (see picture). The incisor is the tooth just to the right or left of your two front teeth.
- Place the flat side of the Striant® system on your fingertip. Gently push the curved side of Striant® against your upper gum in the area shown. Push the Striant® system up as high as it will go on the gum. If you have applied Striant® correctly, the flat side will be facing your cheek.
- Using your finger on the outside of your upper lip, hold the Striant® buccal system in place for 30 seconds (see picture). This will make the buccal system stick to your gum or cheek.
- As the Striant® buccal system absorbs moisture from your mouth, it will begin to soften and will mold to the shape of your gum. You should be aware that Striant® does not dissolve completely, but will remain in place for 12 hours. Striant® is made to stay in place until you remove it.
- Remove Striant® by gently sliding it to the front or back of your mouth to loosen it. Then slide it downwards from your gum to your tooth. This will avoid scratching the gum.
- With each application, you should rotate Striant® to alternate sides of your mouth.
- If Striant® does not stick or falls off within the first 8 hours , remove the original system and apply a new one. This counts as replacing the first dose. Apply the next system about 12 hours after the original buccal system was applied.
- If Striant® falls off after 8 hours but before 12 hours , replace the original buccal system. This replacement can serve as the second dose for that day.
- If Striant® sticks to your cheek and not your gum, this is acceptable. Do not replace the buccal system if this should happen.
- Check to see if Striant® is in place following toothbrushing, use of mouthwash and consumption of food or alcoholic/nonalcoholic beverages. If Striant® does not stick or falls off, follow the above mentioned directions to replace with a new system.

What are the possible side effects of testosterone replacement therapy?

Inform your doctor immediately if any of the following symptoms appear while using Striant®.

- Liver problems. Tell your doctor if:
  - Your skin or white part of your eyes turns yellow (jaundice).
  - Your urine turns dark.
  - Your bowel movements (stool) turns light in color.
  - You don't feel like eating for several days or longer.
  - You feel sick to your stomach (nausea).
  - You have lower abdominal pain (stomach).
- Problems urinating. Tell your doctor if you develop problems urinating while using Striant®. Older patients who use testosterone replacement therapies may have an increased chance of developing prostate enlargement or prostate cancer.
- Extra fluid in the body (edema). Edema can be dangerous if you have heart, kidney or liver problems. Tell your doctor if your ankles and legs swell or if you put on weight quickly.
- Breathing problems, including a sleep problem called "sleep apnea". Sleep apnea is when you stop breathing for short times while you are sleeping. This happens more in patients who are overweight or who have lung disease. Tell your doctor if you have breathing problems or if you or your partner notice changes in your breathing when you are sleeping.
- Penile erections that are painful, that occur too frequently, or that last for too long a duration.
- Breast enlargement - which sometimes does not go away.
- Emotional changes - such as depression.

Your doctor may do blood tests to check your red blood cells, liver function, cholesterol levels, testosterone levels and prostate (PSA) while you are using Striant®, to see how Striant® is affecting your body.

Striant® may also cause these side effects:

- redness, irritation, swelling and pain at the gum application site.
- gum infection (gingivitis)-gum side effects are usually temporary, and should resolve within several days. However, some gum side effects may last up to two weeks. If you should have gum side effects, they usually resolve while taking Striant®. Any abnormal finding should be brought to the attention of your physician.
- a change in how food tastes to you, a bitter taste in your mouth, or an unusual taste in your mouth.
- headache.

These are not all the possible side effects of Striant®. For more information, ask your doctor or pharmacist.

You should regularly examine your gums where Striant® is applied. Any abnormal finding should be brought to the attention of your physician.

How should Striant® be stored?

Keep Striant® at a temperature between 68° and 77° F (20-25° C). Protect from heat and moisture. Do not use a damaged blister package. Keep Striant® and all medicines out of the reach of children. Discarded Striant® buccal systems should be thrown away in a household trash can in a way that prevents children or pets from accidentally using or taking them.

General information about the safe and effective use of Striant®. Medicines are sometimes prescribed for conditions that are not mentioned in patient information leaflets. Do not use Striant® for a condition for which it was not prescribed. Do not give Striant® to other people, even if they have the same symptoms you have. It may harm them, and you should be aware that Striant® is a controlled substance.

This leaflet summarizes the most important information about Striant®. If you would like more information, talk with your doctor. You can ask your doctor or pharmacist for information about Striant® that is written for health professionals.

What are the ingredients of Striant®?

Active Ingredient: Testosterone USP (30 mg in each buccal system)

Inactive Ingredients: anhydrous lactose NF, carbomer 934P, hypromellose USP, magnesium stearate NF, lactose monohydrate NF, polycarbophil USP, colloidal silicon dioxide NF, starch NF, and talc USP.

How is Striant® supplied?

Striant® is supplied in a transparent blister in a white card. Each card contains 10 buccal systems. There are a total of 6 blister cards (60 buccal systems) in each carton.

Rx Only

Manufactured by: Mipharm S.p.A, Milan, Italy

Manufactured for: Columbia Laboratories, Inc., Livingston, NJ 07039

US Patent Numbers: 6,248,358

others pending

© 2003 Columbia Laboratories, Inc.

PATSTN002/41005010002
USA/930874/0

PRINCIPAL DISPLAY PANEL - 60 Buccal System Carton

STRIANT®
CIII
(testosterone buccal system)
mucoadhesive
30mg

NDC 55056-3060-1

6 blister cards
Total 60 buccal systems

Each buccal system
contains
30mg of testosterone

FOR USE IN THE BUCCAL MUCOSA

COLUMBIA
LABORATORIES